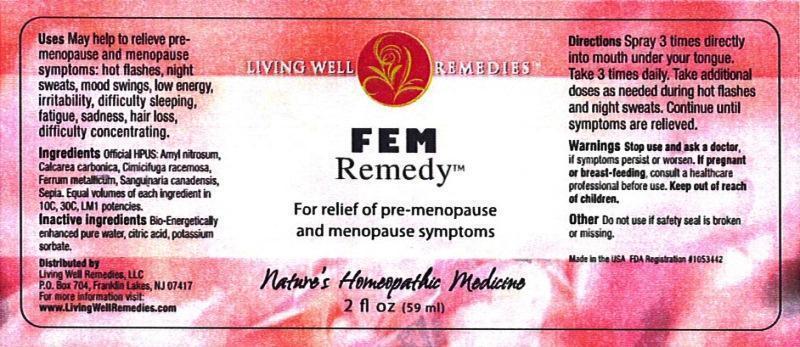 DRUG LABEL: FEM Remedy
NDC: 53852-0008 | Form: LIQUID
Manufacturer: Living Well Remedies, LLC
Category: homeopathic | Type: HUMAN OTC DRUG LABEL
Date: 20140416

ACTIVE INGREDIENTS: AMYL NITRITE 10 [hp_C]/59 mL; OYSTER SHELL CALCIUM CARBONATE, CRUDE 10 [hp_C]/59 mL; BLACK COHOSH 10 [hp_C]/59 mL; IRON 10 [hp_C]/59 mL; SANGUINARIA CANADENSIS ROOT 10 [hp_C]/59 mL; SEPIA OFFICINALIS JUICE 10 [hp_C]/59 mL
INACTIVE INGREDIENTS: WATER; CITRIC ACID MONOHYDRATE; POTASSIUM SORBATE

FEM Remedy

DOSAGE AND ADMINISTRATION

Directions: Spray 3 times directly into mouth under your tongue. Take 3 times daily. Take additional doses as needed during hot flashes and night sweats. Continue until symptoms are relieved.

WARNINGS

Warnings: Stop use and ask a doctor, if symptoms persist or worsen. If pregnant or breast-feeding, consult a healthcare professional before use.

Keep out of reach of children.

OTHER SAFETY INFORMATION

Other: Do not use if safety seal is broken or missing.

PURPOSE

Uses: May help to relieve premenopause and menopause symptoms: hot flashes, night sweats, mood swings, low energy, irritability, difficulty sleeping, fatigue, sadness, hair loss, difficulty concentrating.

ACTIVE INGREDIENT

Ingredients: Official HPUS:Amyl nitrosum, Calcarea carbonica, Cimicifuga racemosa, Ferrum metallicum, Sanguinaria canadensis, Sepia. Equal volumes of each ingredient in 10C, 30C, LM1 potencies.

INACTIVE INGREDIENT

Inactive ingredients: Bio-Energetically enhanced pure water, citric acid, potassium sorbate.

INDICATIONS AND USAGE

Uses: May help to relieve premenopause and menopause symptoms:

- hot flashes
- night sweats
- mood swings
- low energy
- irritability
- difficulty sleeping
- fatigue
- sadness
- hair loss
- difficulty concentrating

PACKAGE LABEL

Distributed by

Living Well Remedies LLC

P.O. Box 704,

Franklin Lakes, NJ 07417

For more information visit:

www.livingWellRenedies.com